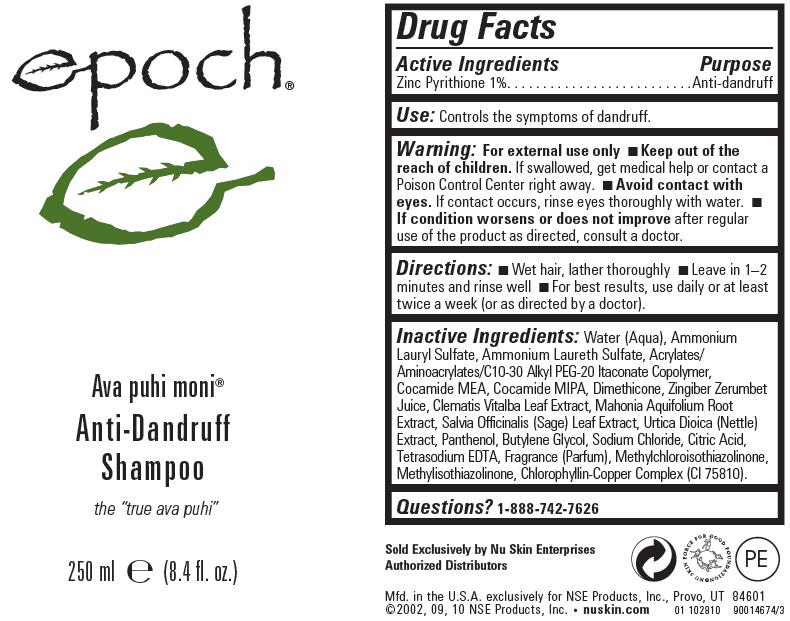 DRUG LABEL: Epoch 
NDC: 62839-2810 | Form: SHAMPOO
Manufacturer: NSE Products, Inc.
Category: otc | Type: HUMAN OTC DRUG LABEL
Date: 20110606

ACTIVE INGREDIENTS: Pyrithione Zinc 10 mL/1000 mL
INACTIVE INGREDIENTS: Water; Ammonium Lauryl Sulfate; Coco Monoethanolamide; Dimethicone; Clematis Vitalba Leaf; Mahonia Aquifolium Root; Sage; Urtica Dioica; Panthenol; Butylene Glycol; Sodium Chloride; Citric Acid Monohydrate; Edetate Sodium; Methylchloroisothiazolinone; Methylisothiazolinone; Sodium Copper Chlorophyllin

epoch®
Ava puhi moni®
Anti-Dandruff
Shampoo

Drug Facts

Active Ingredients

Zinc Pyrithione 1%

Purpose

Anti-dandruff

Use

Controls the symptoms of dandruff.

Warning

For external use only

KEEP OUT OF REACH OF CHILDREN

- Keep out of the reach of children. If swallowed, get medical help or contact a Poison Control Center right away.

WHEN USING

- Avoid contact with eyes. If contact occurs, rinse eyes thoroughly with water.

ASK DOCTOR

- If condition worsens or does not improve after regular use of the product as directed, consult a doctor.

Directions

- Wet hair, lather thoroughly
- Leave in 1–2 minutes and rinse well
- For best results, use daily or at least twice a week (or as directed by a doctor).

Inactive Ingredients

Water (Aqua), Ammonium Lauryl Sulfate, Ammonium Laureth Sulfate, Acrylates/Aminoacrylates/C10-30 Alkyl PEG-20 Itaconate Copolymer, Cocamide MEA, Cocamide MIPA, Dimethicone, Zingiber Zerumbet Juice, Clematis Vitalba Leaf Extract, Mahonia Aquifolium Root Extract, Salvia Officinalis (Sage) Leaf Extract, Urtica Dioica (Nettle) Extract, Panthenol, Butylene Glycol, Sodium Chloride, Citric Acid, Tetrasodium EDTA, Fragrance (Parfum), Methylchloroisothiazolinone, Methylisothiazolinone, Chlorophyllin-Copper Complex (CI 75810).

Questions?

1-888-742-7626

PRINCIPAL DISPLAY PANEL - 250 ml Bottle Label

epoch®

Ava puhi moni®

Anti-Dandruff
Shampoo

the "true ava puhi"

250 ml e (8.4 fl. oz.)